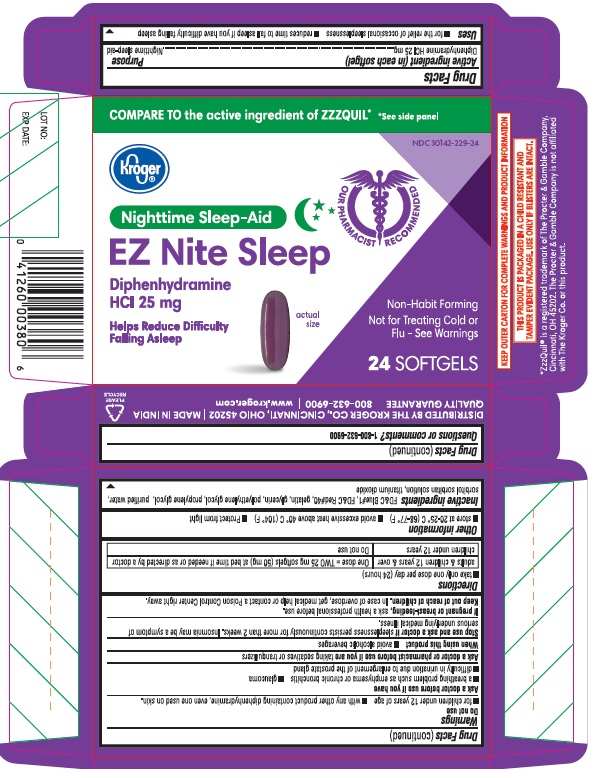 DRUG LABEL: EZ NITE SLEEP
NDC: 30142-229 | Form: CAPSULE
Manufacturer: THE KROGER CO.
Category: otc | Type: HUMAN OTC DRUG LABEL
Date: 20241220

ACTIVE INGREDIENTS: DIPHENHYDRAMINE HYDROCHLORIDE 25 mg/1 1
INACTIVE INGREDIENTS: FD&C BLUE NO. 1; FD&C RED NO. 40; GELATIN; GLYCERIN; POLYETHYLENE GLYCOL, UNSPECIFIED; PROPYLENE GLYCOL; WATER; SORBITOL; TITANIUM DIOXIDE

Kroger® NIGHTTIME SLEEP-AID
EZ NITE SLEEP

Drug Facts

ACTIVE INGREDIENT (in each softgel)

Diphenhydramine HCl 25mg

Purpose

Nighttime sleep-aid

Uses

- for the relief of occasional sleeplessness
- reduces time to fall asleep if you have difficulty falling asleep

Drug Facts (continued)

Warnings

Do not use

- for children under 12 years of age
- with any other product containing diphenhydramine, even one used on skin.

Ask a doctor before use if you have

- a breathing problem such as emphysema or chronic bronchitis
- glaucoma
- difficulty in urination due to enlargement of prostate gland

Ask a doctor or pharmacist before use if you are taking sedatives or tranquilizers

When using this product

- avoid alcoholic beverages

Stop use and ask a doctor if sleeplessness persists continously for more than 2 weeks. Insomnia may be a symptom be a symptom of serious underlying medical illness.

PREGNANCY OR BREAST FEEDING

If pregnant of breast-feeding, ask a health professional before use.

Keep out of reach of children. In care of overdose, get medical help or contact a Poison Control Center right away.

Directions

- take only one dose per day (24 hours)

adults & children 12 years & over | One dose= TWO 25 mg softgels (50 mg) at bed time if needed or as directed by a doctor
children under 12 years | Do not use

Other information

- Store at 20-25° C (68-77° F)
- avoid excessive heat above 40° C (104° F)
- Protect from light

Inactive ingredients

FD&C Blue#1, FD&C Red#40, gelatin, glycerin, polyethylene glycol, propylene glycol, purified water, sorbitol sorbitan solution, titanium dioxide

Drug Facts (continued)

Questions or comments? 1-800-632-6900

PRINCIPAL DISPLAY PANEL

COMPARE TO the active ingredient of ZZZQUIL® *see side panel

NDC 30142-229-24

Kroger®

Nighttime Sleep-Aid

EZ Nite Sleep

Diphenhydramine HCL 25 mg

Helps Reduce Difficulty Faling Asleep

actual size

Non-Habit Forming

Not fro Treating Cold or Flu- See Warnings

24 SOFTGELS

*Zzzquil® is a registered trademark of The Procter & Gamble Company, Cincinnati, OH 45202. The Procter & Gamble Comopany is not affiliated with The Kroger Co. ir this product.